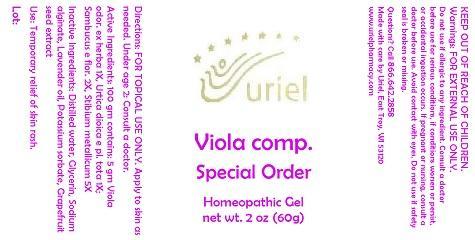 DRUG LABEL: Viola comp. Special Order
NDC: 48951-9047 | Form: GEL
Manufacturer: Uriel Pharmacy Inc.
Category: homeopathic | Type: HUMAN OTC DRUG LABEL
Date: 20141104

ACTIVE INGREDIENTS: VIOLA ODORATA FLOWERING TOP 1 [hp_X]/1 g; URTICA DIOICA 1 [hp_X]/1 g; SAMBUCUS NIGRA FLOWERING TOP 2 [hp_X]/1 g; ANTIMONY 5 [hp_X]/1 g
INACTIVE INGREDIENTS: WATER; GLYCERIN; SODIUM ALGINATE; LAVENDER OIL; POTASSIUM SORBATE; CITRUS PARADISI SEED

Viola comp. Special Order

INDICATIONS AND USAGE

Directions: FOR TOPICAL USE ONLY.

DOSAGE AND ADMINISTRATION

Apply to skin as needed. Under age 2: Consult a doctor.

ACTIVE INGREDIENT

Active Ingredients: 100 gm contains: 5 gm Viola odor. ex herba 1X, Urtica dioica e pl. tota 1X; Sambucus e flor. 2X, Stibium metallicum 5X

INACTIVE INGREDIENT

Inactive Ingredients: Distilled water, Glycerin, Sodium alginate, Lavender oil, Potassium sorbate, Grapefruit seed extract

PURPOSE

Use: Temporary relief of skin rash.

KEEP OUT OF REACH OF CHILDREN.

WARNINGS

Warnings: FOR EXTERNAL USE ONLY. Do not use if allergic to any ingredient. Consult a doctor before use for serious conditions, if conditions worsen or persist, or accidental ingestion occurs. If pregnant or nursing, consult a doctor before use. Avoid contact with eyes. Do not use if safety seal is broken or missing.

QUESTIONS

Questions? Call 866.642.2858 Made with care by Uriel, East Troy, WI 53120 www.urielpharmacy.com